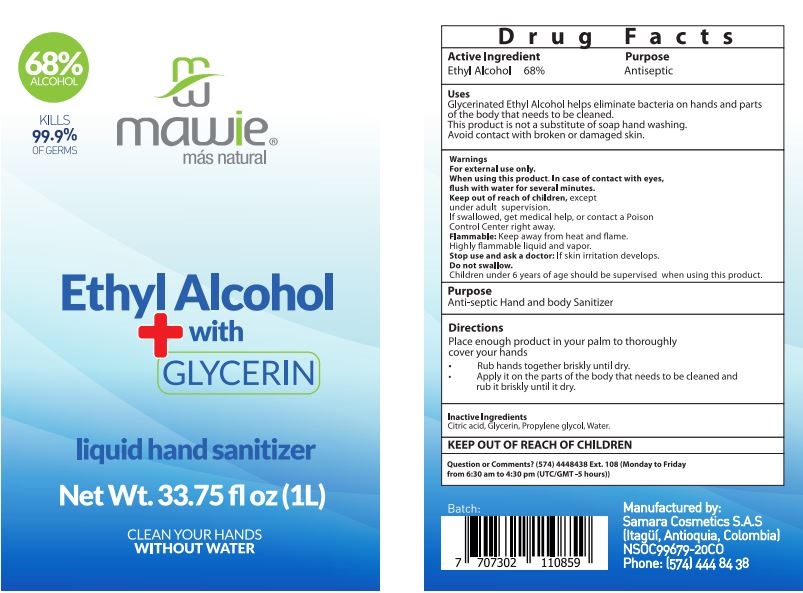 DRUG LABEL: Hand Sanitizer
NDC: 79894-008 | Form: LIQUID
Manufacturer: SAMARA COSMETICS S.A.S.
Category: otc | Type: HUMAN OTC DRUG LABEL
Date: 20200801

ACTIVE INGREDIENTS: ALCOHOL 68 mL/100 mL
INACTIVE INGREDIENTS: CITRIC ACID MONOHYDRATE 0.05 mL/100 mL; GLYCERIN 2 mL/100 mL; PROPANEDIOL 0.5 mL/100 mL; WATER 29.45 mL/100 mL

HAND SANITIZER LIQUID

This is a hand sanitizer manufactured according to the Temporary Policy for Preparation of Certain Alcohol-Based Hand Sanitizer Products During the Public Health Emergency (CoViD-19); Guidance for Industry.

The hand sanitizer is manufactured using only the following United States Pharmacopoeia (USP) grade ingredients in the preparation of the product (percentage in final product formulation) consistent with World Health Organization (WHO) recommendations:

1. Alcohol (ethanol) (USP or Food Chemical Codex (FCC) grade) (80%, volume/volume (v/v)) in an aqueous solution denatured according to Alcohol and Tobacco Tax and Trade Bureau regulations in 27 CFR part 20.
2. Glycerol (1.45% v/v).
3. Hydrogen peroxide (0.125% v/v).
4. Sterile distilled water or boiled cold water.

The firm does not add other active or inactive ingredients. Different or additional ingredients may impact the quality and potency of the product.

Active Ingredient(s)

Alcohol 68% v/v. Purpose: Antiseptic

Purpose

Antiseptic, Hand Sanitizer

Use

* Helps eliminate bacteria on the hand and parts of the body that needs to be cleaned. This product is not a substitute of soap hand washing. Avoid contact with broken or damaged skin

Warnings

- For external use only-
- When using this product keep out o f eyes. In case of contact, flush with water several minutes.
- Keep out of reach of children except under adult supervision
- If swalow get medical help or contact a Poison Control Center right away.
- Flammable: Keep away from heat and flame.
- Stop use and ask Doctor: if skin irritation develops.
- Do not swalow
- Children under 6 years old should be supervised when using this product

Do not use

Stop use and ask a doctor if

* Irritation develops

When using this product keep out of eyes, ears, and mouth. In case of contact with eyes, rinse eyes thoroughly with water.
Stop use and ask a doctor if irritation or rash occurs. These may be signs of a serious condition.
Keep out of reach of children. If swallowed, get medical help or contact a Poison Control Center right away.

Stop use and ask a doctor if irritation or rash occurs. These may be signs of a serious condition.

Keep out of reach of children. If swallowed, get medical help or contact a Poison Control Center right away.

Directions

- Place enough product in your palm to throughly cover your hands.
- Rub hands together briskly until dry
- Apply it on the parts of the body that needs to be cleaned and rub it briskly until dry

Other information

QUESTIONS OR COMMENTS: (574) 4448438 Ext 108 (Monday to Friday) 6:30 am to 4:30 pm (UTC/GMT 5 hours)

Inactive ingredients

glycerin, water. citric acid, propanediol